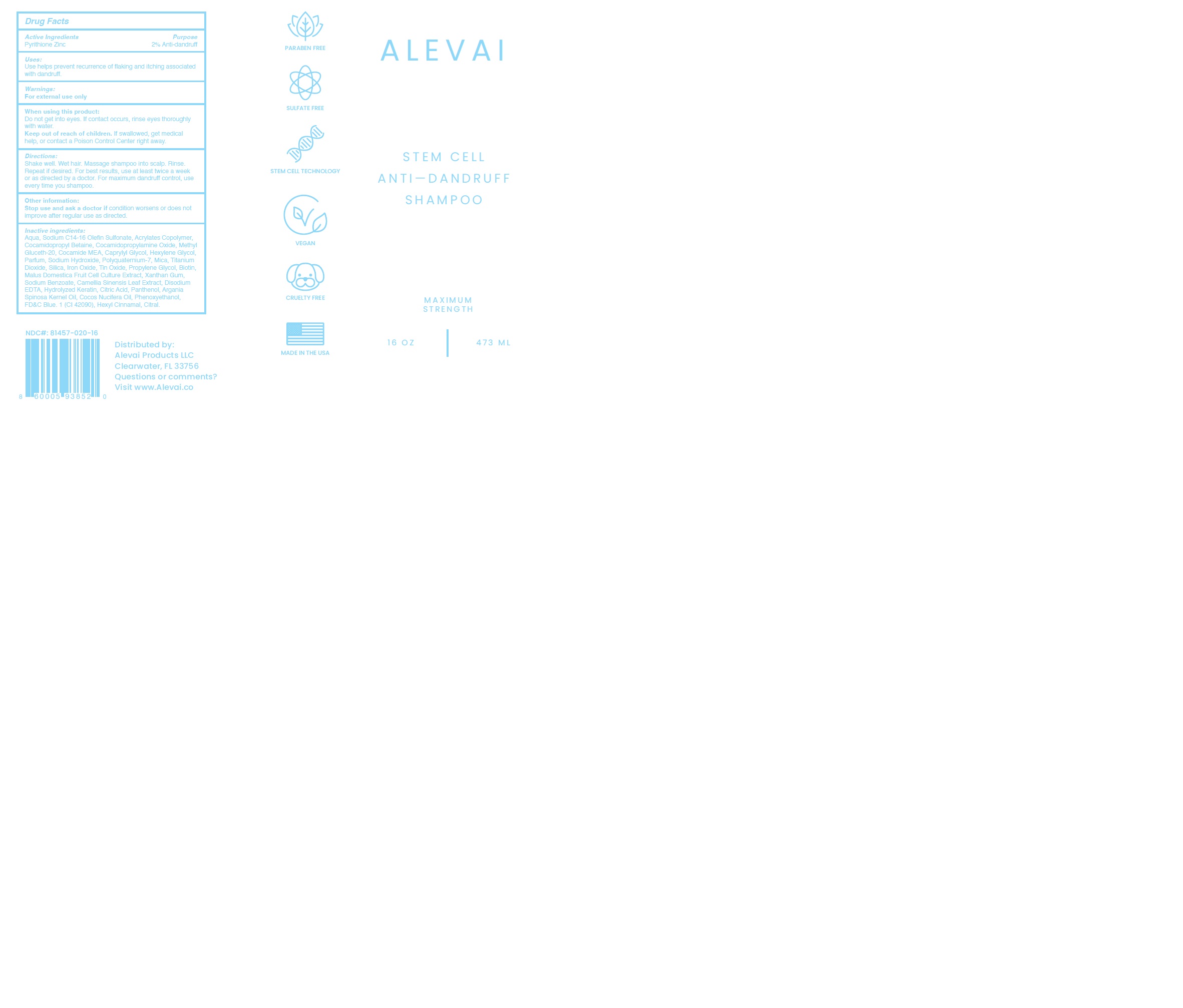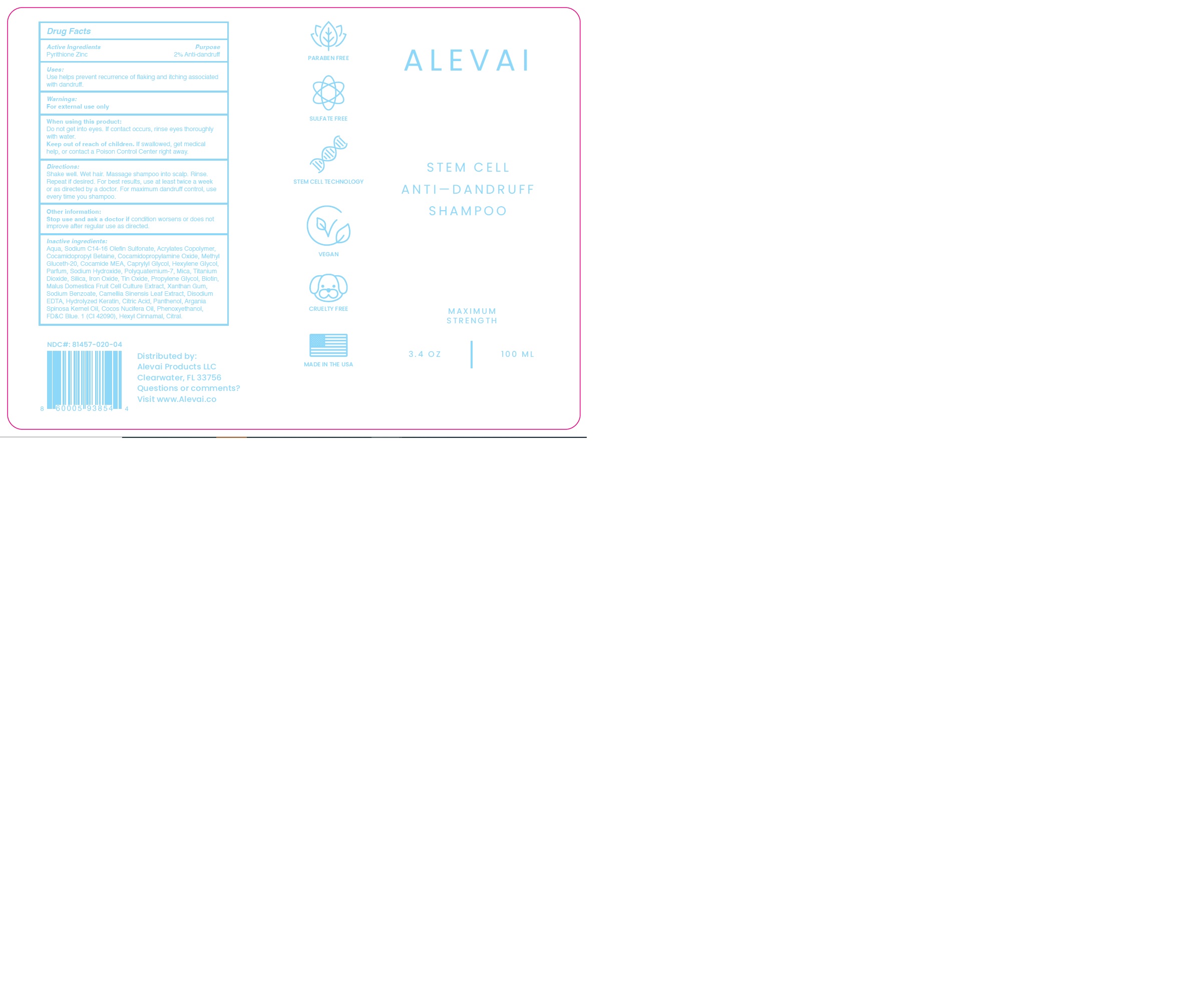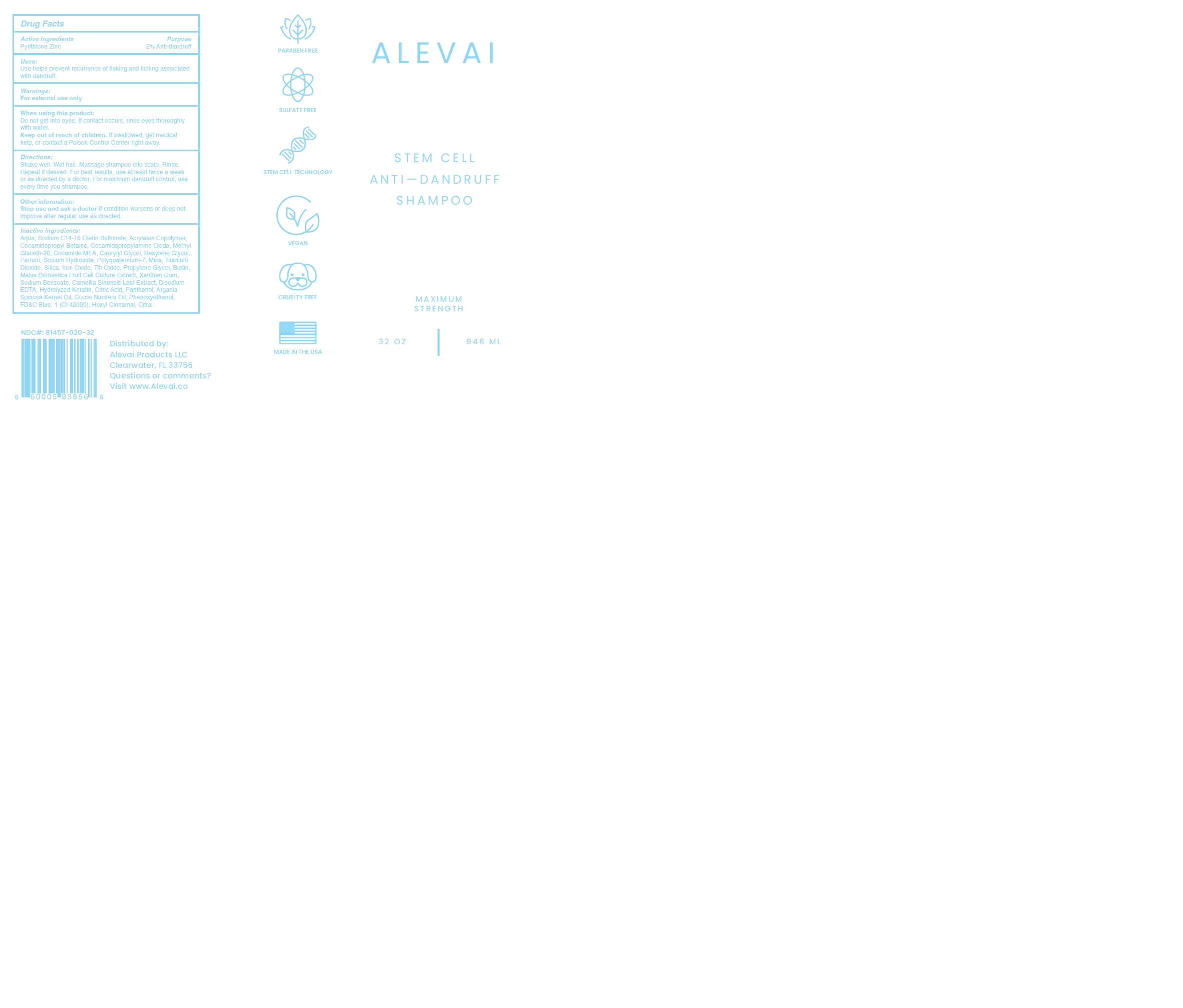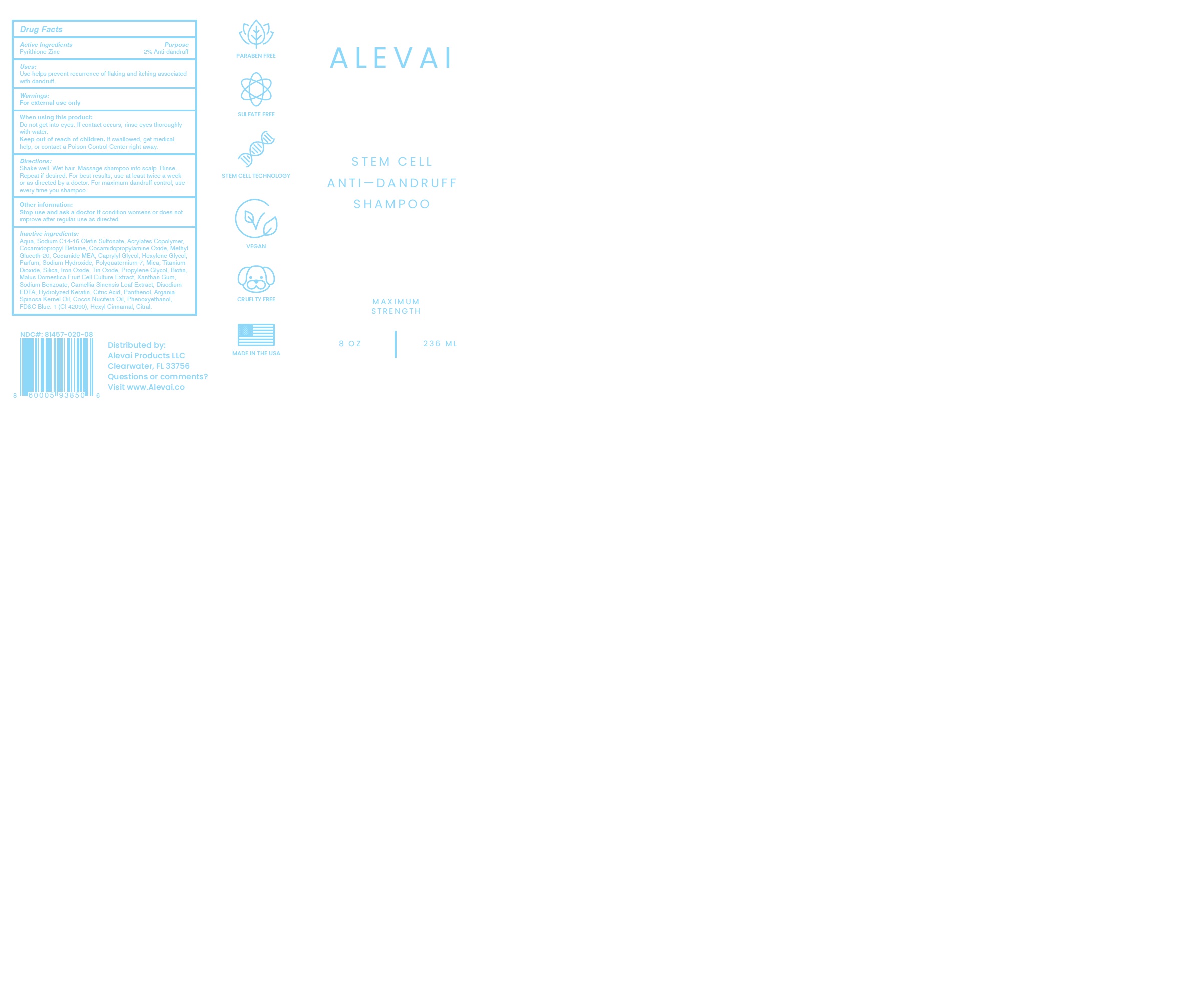 DRUG LABEL: ALEVAI - STEM CELL ANTI DANDRUFF
NDC: 81457-020 | Form: SHAMPOO
Manufacturer: ALEVAI PRODUCTS LLC
Category: otc | Type: HUMAN OTC DRUG LABEL
Date: 20241122

ACTIVE INGREDIENTS: PYRITHIONE ZINC 2 g/100 g
INACTIVE INGREDIENTS: COCO MONOETHANOLAMIDE; PROPYLENE GLYCOL; MICA; TITANIUM DIOXIDE; COCAMIDOPROPYLAMINE OXIDE; STANNIC OXIDE; ARGANIA SPINOSA WHOLE; XANTHAN GUM; COCAMIDOPROPYL BETAINE; CAPRYLYL GLYCOL; PHENOXYETHANOL; FD&C BLUE NO. 1; PANTHENOL; COCOS NUCIFERA WHOLE; SODIUM C14-16 OLEFIN SULFONATE; METHYL GLUCETH-20; BIOTIN; CAMELLIA SINENSIS FLOWER; SILICON DIOXIDE; WATER; HEXYLENE GLYCOL; POLYQUATERNIUM-7 (70/30 ACRYLAMIDE/DADMAC; 1600 KD); SODIUM HYDROXIDE; SODIUM BENZOATE; MALUS DOMESTICA WHOLE; EDETATE DISODIUM; ANHYDROUS CITRIC ACID

81457-020-04
81457-020-08
81457-020-16
81457-020-32

ACTIVE INGREDIENT

Pyrithione Zinc………………………………………………………………………………………. 2% Anti-dandruff

PURPOSE

Use helps prevent recurrence of flaking and itching associated with dandruff.

When using this product do not get into eyes. If contact occurs, rinse eyes thoroughly with water.

WARNINGS

For external use only.

When using this product do not get into eyes. If contact occurs, rinse eyes thoroughly with water.

Keep out of reach of children. If swallowed, get medical help, or contact a Poison Control Center right away.

DOSAGE AND ADMINISTRATION

Shake well. Wet hair. Massage shampoo into scalp. Rinse. Repeat if desired. For best results, use at least twice a week or as directed by a doctor. For maximum dandruff control, use every time you shampoo.

Stop use and ask a doctor if condition worsens or does not improve after regular use as directed.

INACTIVE INGREDIENT

Aqua, Sodium C14-16 Olefin Sulfonate, Acrylates Copolymer, Cocamidopropyl Betaine, Cocamidopropylamine Oxide, Methyl Gluceth-20, Cocamide MEA, Caprylyl Glycol, Hexylene Glycol, Parfum, Sodium Hydroxide, Polyquaternium-7, Mica, Titanium Dioxide, Silica, Iron Oxide, Tin Oxide, Propylene Glycol, Biotin, Malus Domestica Fruit Cell Culture Extract, Xanthan Gum, Sodium Benzoate, Camellia Sinensis Leaf Extract, Disodium EDTA, Hydrolyzed Keratin, Citric Acid, Panthenol, Argania Spinosa Kernel Oil, Cocos Nucifera Oil, Phenoxyethanol, FD&C Blue. 1 (CI 42090), Hexyl Cinnamal, Citral.